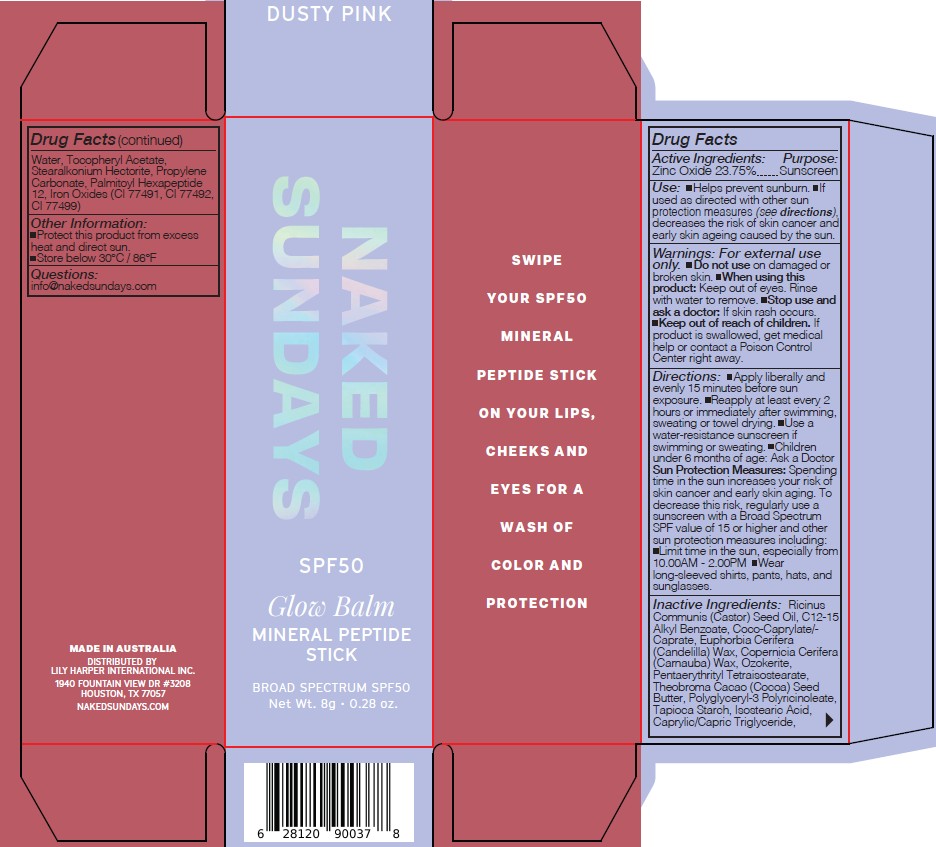 DRUG LABEL: Naked Sundays Glow Balm Mineral Peptide Stick Broad Spectrum SPF50 Dusky Pink 8g
NDC: 81104-105 | Form: STICK
Manufacturer: NAKED SUNDAYS PTY LTD
Category: otc | Type: HUMAN OTC DRUG LABEL
Date: 20251117

ACTIVE INGREDIENTS: ZINC OXIDE 23.75 g/100 g
INACTIVE INGREDIENTS: CERESIN; CI 77491; STEARALKONIUM HECTORITE; COPERNICIA CERIFERA (CARNAUBA) WAX; THEOBROMA CACAO (COCOA) SEED BUTTER; PALMITOYL HEXAPEPTIDE-12; CI 77499; COCO-CAPRYLATE/CAPRATE; C12-15 ALKYL BENZOATE; .ALPHA.-TOCOPHEROL ACETATE; TAPIOCA STARCH; POLYGLYCERYL-3 PENTARICINOLEATE; ISOSTEARIC ACID; RICINUS COMMUNIS (CASTOR) SEED OIL; PENTAERYTHRITYL TETRAISOSTEARATE; EUPHORBIA CERIFERA (CANDELILLA) WAX; FERRIC OXIDE YELLOW; PROPYLENE CARBONATE; CAPRYLIC/CAPRIC TRIGLYCERIDE

Naked Sundays Glow Balm Mineral Peptide Stick Broad Spectrum SPF50 Dusky Pink 8g

Active Ingredients:

Zinc Oxide 23.75 %

INACTIVE INGREDIENT

INACTIVE INGREDIENTS: C12-15 Alkyl Benzoate, Caprylic/Capric Triglyceride, Coco-Caprylate/Caprate, Copernicia Cerifera (Carnauba) Wax, Euphorbia Cerifera (Candelilla) Wax, Iron Oxides (CI77491, CI77492, CI 77499), Isostearic Acid, Palmitoyl Hexapeptide-12, Pentaerythrityl Tetraisostearate, Polyglyceryl-3 Polyricinoleate, Propylene Carbonate, Ricinus Communis (Castor) Seed Oil, Stearalkonium Hectorite, Tapioca Starch, Theobroma Cacao (Cocoa) Seed Butter, Tocopheryl Acetate,OZOKERITE

INDICATIONS AND USAGE

Use: Helps prevent sunburn. If
used as directed with other sun
protection measures (see directions),
decreases the risk of skin cancer and
early skin ageing caused by the sun.

Keep out of reach of children.

Warnings: For external use
only. Do not use on damaged or
broken skin. When using this
product: Keep out of eyes. Rinse
with water to remove. Stop use and
ask a doctor: If skin rash occurs.
Keep out of reach of children. If
product is swallowed, get medical
help or contact a Poison Control
Center right away.

USER SAFETY WARNINGS

Directions: Apply liberally and
evenly 15 minutes before sun
exposure. Reapply at least every 2
hours or immediately after swimming,
sweating or towel drying. Use a
water-resistance sunscreen if
swimming or sweating. Children
under 6 months of age: Ask a Doctor
Sun Protection Measures: Spending
time in the sun increases your risk of
skin cancer and early skin aging. To
decrease this risk, regularly use a
sunscreen with a Broad Spectrum
SPF value of 15 or higher and other
sun protection measures including:
Limit time in the sun, especially from
10.00AM - 2.00PM Wear
long-sleeved shirts, pants, hats, and
sunglasses.

Other Information:
Protect this product from excess
heat and direct sun.
Store below 30°C / 86°F

Questions:
info@nakedsundays.com

PURPOSE

SPF Sunscreen

DOSAGE AND ADMINISTRATION

Directions: Apply liberally and
evenly 15 minutes before sun
exposure. Reapply at least every 2
hours or immediately after swimming,
sweating or towel drying. Use a
water-resistance sunscreen if
swimming or sweating.